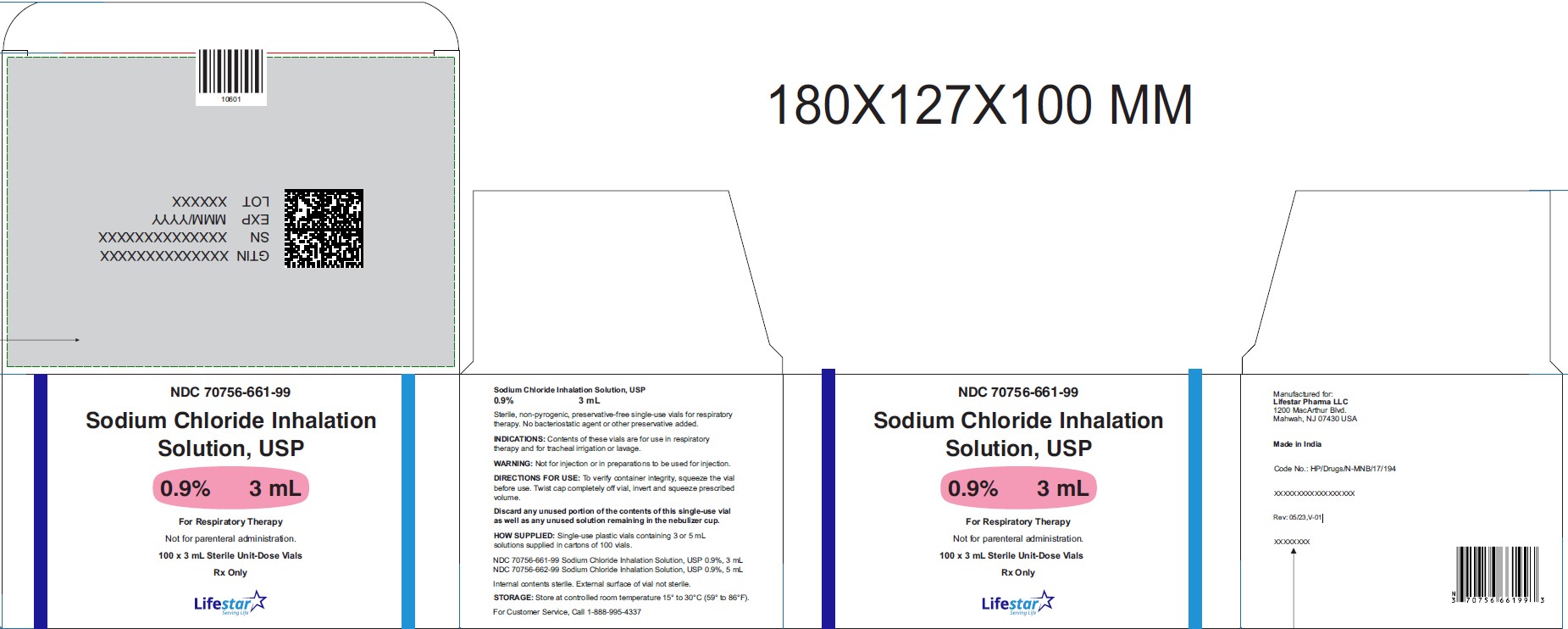 DRUG LABEL: Sodium Chloride
NDC: 70756-661
Manufacturer: Lifestar Pharma LLC
Category: other | Type: MEDICAL DEVICE
Date: 20260210

ACTIVE INGREDIENTS: SODIUM CHLORIDE 0.027 g/3 mL

Sodium Chloride Inhalation Solution

Sodium Chloride Inhalation Solution 0.9% 3 mL

NDC 70756-661-99

Sodium Chloride Inhalation
Solution, USP
0.9% 3 mL

For Respiratory Therapy

Not for Parenteral Administration.

100 x 3 mL Sterile Unit-Dose Vials

Rx Only

Sodium Chloride Inhalation Solution, USP
0.9% 3 mL

Sterile, non-pyrogenic, preservative-free single-use vials for respiratory therapy. No bacteriostatic agent or other preservative added.

INDICATIONS: Contents of these vials are for use in respiratory therapy and for tracheal irrigation or lavage.

WARNING: Not for injection or in preparations to be used for injection.

DIRECTIONS FOR USE: To verify container integrity, squeeze the vial before use. Twist cap completely off vial, invert and squeeze prescribed volume.

Discard any unused portion of the contents of this single-use vial as well as any unused solution remaining in the nebulizer cup.

HOW SUPPLIED: Single-use plastic vials containing 3 mL or 5 mL solutions supplied in cartons of 100 vials and 15 mL solution supplied in cartons of 50 vials.

NDC 70756-661-99 Sodium Chloride Inhalation Solution, USP 0.9%, 3 mL
NDC 70756-662-99 Sodium Chloride Inhalation Solution, USP 0.9%, 5 mL

Internal contents sterile. External surface of vial not sterile.

STORAGE: Store at controlled room temperature 15° to 30°C (59° to 86°F).

For Customer Service, Call 1-888-995-4337

Manufactured for:

Lifestar Pharma LLC
1200 MacArthur Blvd.
Mahwah, NJ 07430 USA

Made in India

Rev: 05/23,V-01